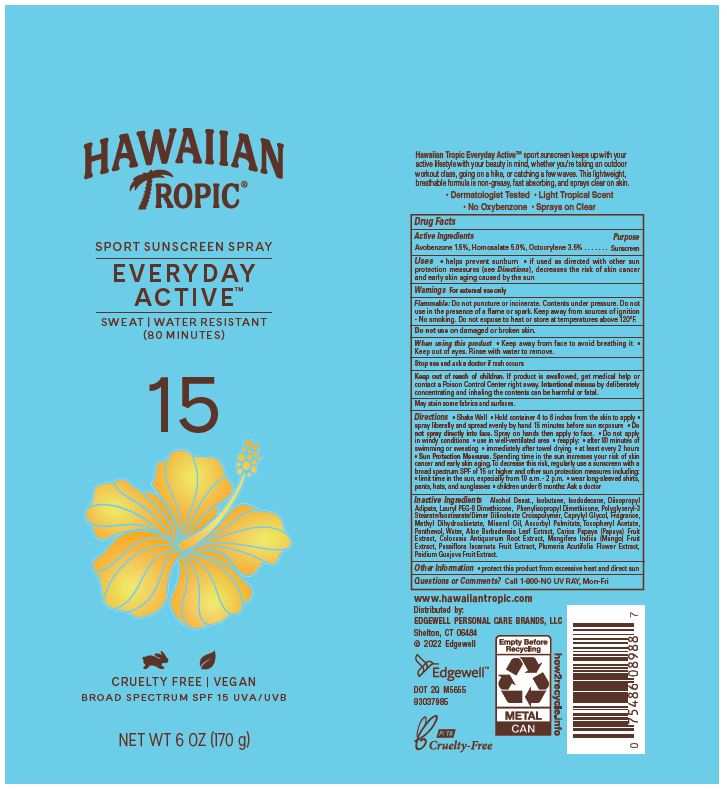 DRUG LABEL: Hawaiian Tropic Sport Sunscreen Everyday Active
NDC: 63354-803 | Form: AEROSOL, SPRAY
Manufacturer: Edgewell Personal Care Brands LLC
Category: otc | Type: HUMAN OTC DRUG LABEL
Date: 20241101

ACTIVE INGREDIENTS: HOMOSALATE 5 g/100 g; OCTOCRYLENE 3.5 g/100 g; AVOBENZONE 1.5 g/100 g
INACTIVE INGREDIENTS: LAURYL PEG-8 DIMETHICONE (300 CPS); DEHYDRATED ALCOHOL; GUAVA; PAPAYA; MINERAL OIL; CAPRYLYL GLYCOL; PANTHENOL; ALOE VERA LEAF; ISODODECANE; DIISOPROPYL ADIPATE; PASSIFLORA INCARNATA FRUIT; ISOBUTANE; COLOCASIA ESCULENTA ROOT; MANGO; PLUMERIA RUBRA FLOWER; WATER; METHYL DIHYDROABIETATE; .ALPHA.-TOCOPHEROL ACETATE; ASCORBYL PALMITATE

Active Ingredients

Avobenzone 1.5%, Homosalate 5.0%, Octocrylene 3.5%

Purpose

Sunscreen

Uses

• helps prevent sunburn • if used as directed with other sun protection measures (see Directions), decreases the risk of skin cancer and early skin aging caused by the sun

Flammable: Do not puncture or incinerate. Contents under pressure. Do not use in the presence of a flame or spark. Keep away from sources of ignition - No smoking. Do not expose to heat or store at temperatures above 120°F.

May stain some fabrics and surfaces.

Warnings

For external use only

Do not use

on damaged or broken skin.

When using this product

Keep away from face to avoid breathing it • Keep out of eyes. Rinse with water to remove.

Stop use and ask a doctor

if rash occurs

Keep out of reach of children.

If product is swallowed, get medical help or contact a Poison Control Center right away. Intentional misuse by deliberately concentrating and inhaling the contents can be harmful or fatal.

Direction

• Shake Well • Hold container 4 to 6 inches from the skin to apply • spray liberally and spread evenly by hand 15 minutes before sun exposure • Do not spray directly into face. Spray on hands then apply to face. • Do not apply in windy conditions • use in well-ventilated area • reapply: • after 80 minutes of swimming or sweating • immediately after towel drying • at least every 2 hours • Sun Protection Measures. Spending time in the sun increases your risk of skin cancer and early skin aging. To decrease this risk, regularly use a sunscreen with a broad spectrum SPF of 15 or higher and other sun protection measures including: • limit time in the sun, especially from 10 a.m. - 2 p.m. • wear long-sleeved shirts, pants, hats, and sunglasses • children under 6 months: Ask a doctor

Inactive Ingredients

Alcohol Denat., Isobutane, Isododecane, Diisopropyl Adipate, Lauryl PEG-8 Dimethicone, Phenylisopropyl Dimethicone, Polyglyceryl-3 Stearate/Isostearate/Dimer Dilinoleate Crosspolymer, Caprylyl Glycol, Fragrance, Methyl Dihydroabietate, Mineral Oil, Ascorbyl Palmitate, Tocopheryl Acetate, Panthenol, Water, Aloe Barbadensis Leaf Extract, Carica Papaya (Papaya) Fruit Extract, Colocasia Antiquorum Root Extract, Mangifera Indica (Mango) Fruit Extract, Passiflora Incarnata Fruit Extract, Plumeria Acutifolia Flower Extract, Psidium Guajava Fruit Extract.

Other Information

• protect this product from excessive heat and direct sun

Questions or Comments?

Call 1-800-NO UV RAY, Mon-Fri

PRINCIPAL DISPLAY PANEL

HAWAIIAN

TROPIC(R)
SPORT SUNSCREEN SPRAY
EVERYDAY
ACTIVE(TM)
SWEAT | WATER RESISTANT
(80 MINUTES)
15
CRUELTY FREE | VEGAN
BROAD SPECTRUM SPF 15 UVA/UVB
NET WT 6 OZ (170 g)